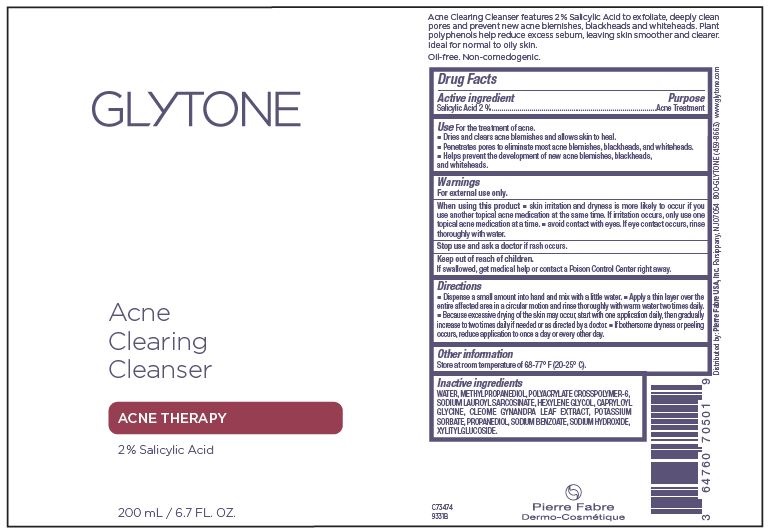 DRUG LABEL: Glytone Acne Clearing Cleanser
NDC: 64760-705 | Form: LIQUID
Manufacturer: Pierre Fabre USA
Category: otc | Type: HUMAN OTC DRUG LABEL
Date: 20240429

ACTIVE INGREDIENTS: SALICYLIC ACID 2 g/100 mL
INACTIVE INGREDIENTS: XYLITYLGLUCOSIDE; SODIUM BENZOATE; METHYLPROPANEDIOL; AMMONIUM ACRYLOYLDIMETHYLTAURATE, DIMETHYLACRYLAMIDE, LAURYL METHACRYLATE AND LAURETH-4 METHACRYLATE COPOLYMER, TRIMETHYLOLPROPANE TRIACRYLATE CROSSLINKED (45000 MPA.S); WATER; CAPRYLOYL GLYCINE; CLEOME GYNANDRA LEAF; POTASSIUM SORBATE; HEXYLENE GLYCOL; SODIUM LAURYL SARCOSINATE; PROPANEDIOL; SODIUM HYDROXIDE

Glytone Acne Clearing Cleanser

Active Ingredients

Salicylic Acid 2%

Purpose

Acne Treament

Use

- Dries and clears acne blemishes and allows skin to heal.
- Penetrates pores to eliminate most acne blemishes, blackheads, and whiteheads.
- Helps prevent the development of new acne blemishes, blackheads, and whiteheads.

Warnings

For external use only.

When using this product

- skin irritation and dryness is more likely to occur if you use another topical acne medication at the same time. If irritation occurs, only use one topical acne medication at a time.
- avoid contact with eyes. If eye contact occurs, rinse thoroughly with water.

Stop use and ask a doctor

if rash occurs.

Keep out of reach of children.

If swallowed, get medical help or contact a Poison Control Center right away.

Directions

- Dispense a small amount into hand and mix with a little water.
- Apply a thin layer over the entire affected area in a circular motion and rinse thoroughly with warm water two times daily.
- Because excessive drying of the skin may occur, start with one application daily, then gradually increase to two times daily if needed or as directed by a doctor.
- If bothersome dryness or peeling occurs, reduce application to once a day or every other day.

Other information

Store at room temperature of 68-77° F (20-25° C).

Inactive ingredients

WATER, METHYLPROPANEDIOL, POLYACRYLATE CROSSPOLYMER-6, SODIUM LAUROYL SARCOSINATE, HEXYLENE GLYCOL, CAPRYLOYL GLYCINE, CLEOME GYNANDRA LEAF EXTRACT, POTASSIUM SORBATE, PROPANEDIOL, SODIUM BENZOATE, SODIUM HYDROXIDE, XYLITYLGLUCOSIDE.

Principal Display Panel 200mL Bottle

GLYTONE

Acne Clearing Cleanser

2% Salicylic Acid

200 mL/6.7 Fl. Oz.